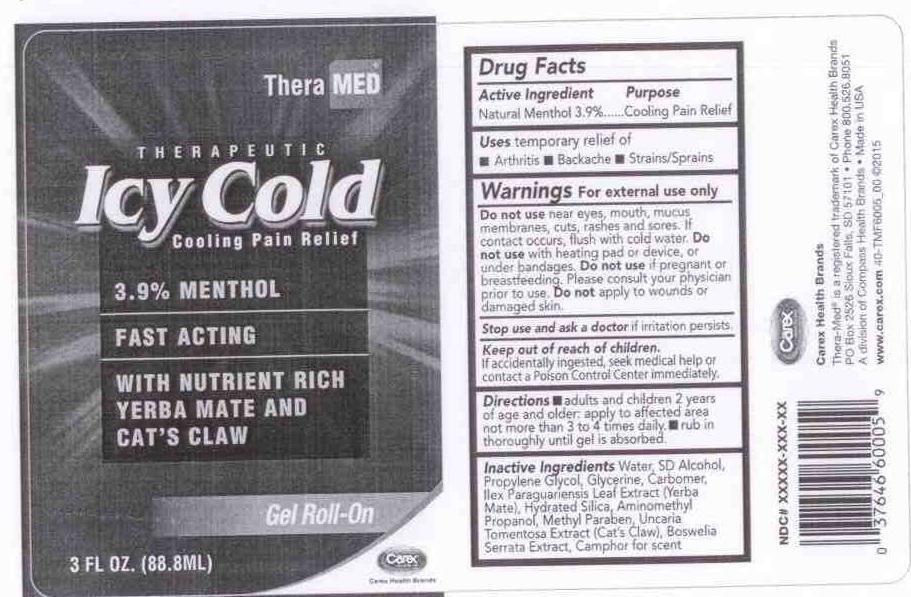 DRUG LABEL: THERAPEUTIC ICY COLD
NDC: 69851-101 | Form: GEL
Manufacturer: APEX-CAREX HEATHCARE PRODUCTS
Category: otc | Type: HUMAN OTC DRUG LABEL
Date: 20191123

ACTIVE INGREDIENTS: MENTHOL 3.9 g/100 mL
INACTIVE INGREDIENTS: WATER; ALCOHOL; PROPYLENE GLYCOL; GLYCERIN; CARBOMER 940; ILEX PARAGUARIENSIS LEAF; HYDRATED SILICA; AMINOMETHYLPROPANOL; METHYLPARABEN; UNCARIA TOMENTOSA LEAF; BOSWELLIA SERRATA RESIN OIL; CAMPHOR OIL

ACTIVE INGREDIENT

NATURAL MENTHOL 3.9%

PURPOSE

COOLING PAIN RELIEF

USES

TEMPORARY RELIEF OF

- ARTHRITIS
- BACKACHE
- STRAINS/SPRAINS

WARNINGS

FOR EXTERNAL USE ONLY.

DO NOT USE NEAR EYES, MOUTH, MUCUS MEMBRANES, CUTS, RASHES AND SORES. IF CONTACT OCCURS, FLUSH WITH COLD WATER.

DO NOT USE WITH HEATING PAD OR DEVICE, OR UNDER BANDAGES.

DO NOT USE IF PREGNANT OR BREASTFEEDING. PLEASE CONSULT YOUR PHYSICIAN PRIOR TO USE.

DO NOT APPLY TO WOUNDS OR DAMAGED SKIN.

STOP USE AND ASK A DOCTOR IF IRRITATION PERSISTS.

KEEP OUT OF REACH OF CHILDREN.

IF ACCIDENTALLY INGESTED, SEEK MEDICAL HELP OR CONTACT A POISON CONTROL CENTER IMMEDIATELY.

DIRECTIONS

- ADULTS AND CHILDREN 2 YEARS OF AGE AND OLDER, APPLY TO AFFECTED AREA NOT MORE THAN 3 TO 4 TIMES DAILY.
- RUB IN THOROUGHLY UNTIL GEL IS ABSORBED.

INACTIVE INGREDIENTS

WATER, SD ALCOHOL, PROPYLENE GLYCOL, GLYCERINE, CARBOMER, ILEX PARAGUARIENSIS LEAF EXTRACT (YERBA MATE), HYDRATED SILICA, AMINOMETHYL PROPANOL, METHYL PARABEN, UNCARIA TOMENTOSA EXTRACT (CAT'S CLAW), BOSWELIA SERRATA EXTRACT, CAMPHOR FOR SCENT